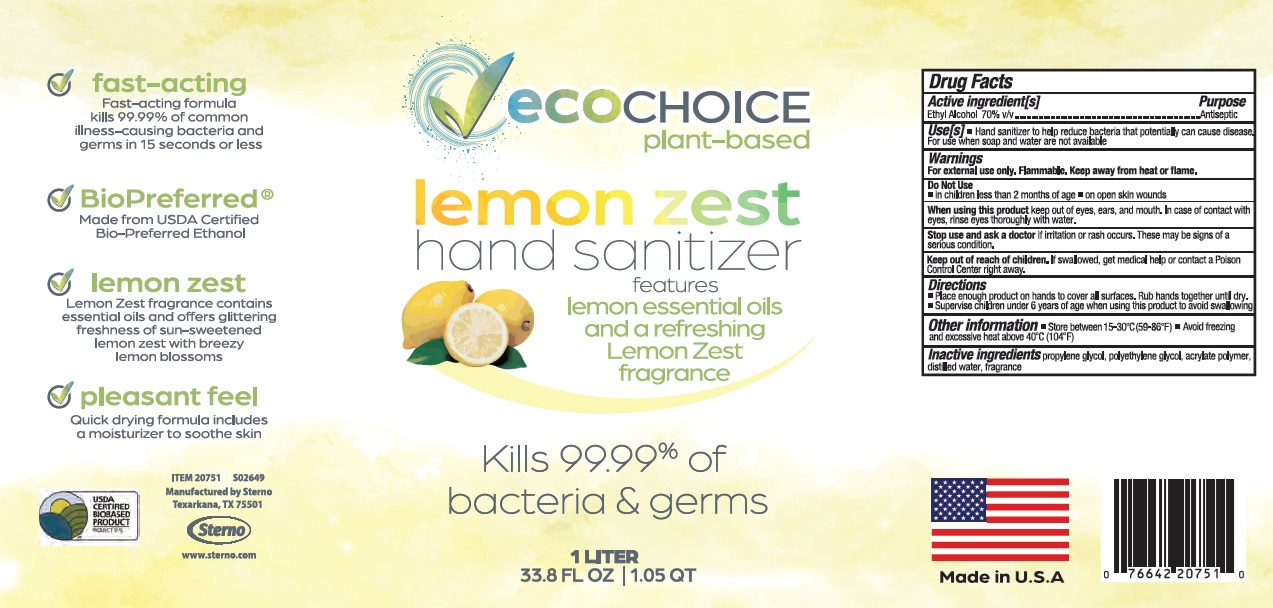 DRUG LABEL: EcoChoice Sterno Hand Sanitizer Lemon Zest
NDC: 73926-753 | Form: SOLUTION
Manufacturer: STERNO PRODUCTS, LLC
Category: otc | Type: HUMAN OTC DRUG LABEL
Date: 20260107

ACTIVE INGREDIENTS: ALCOHOL 70 mL/100 mL
INACTIVE INGREDIENTS: PROPYLENE GLYCOL; POLYETHYLENE GLYCOL, UNSPECIFIED; WATER; RAPIDGEL EZ1

Active Ingredient

Ethanol 70% v/v.

Purpose

Antiseptic

Use

Hand Sanitizer to help reduce bacteria that potentially can cause disease. For use when soap and water are not available.

Warnings

For external use only. Flammable. Keep away from heat or flame

Do not use

- in children less than 2 months of age
- on open skin wounds

When using this product keep out of eyes, ears, and mouth. In case of contact with eyes, rinse eyes thoroughly with water.
Stop use and ask a doctor ifirritation or rash occurs. These may be signs of a serious condition.

Keep out of reach of children.If swallowed, get medical help or contact a Poison Control Center right away.

Stop use and ask a doctor

If irritation or rash occurs, These may be signs of a serious condition

Directions

- Place enough product on hands to cover all surfaces. Rub hands together until dry.
- Supervise children under 6 years of age when using this product to avoid swallowing.

Other information

- Store between 15-30oC (59-86oF)
- Avoid freezing and excessive heat above 40oC (104oF)

Inactive ingredients

Propylene glycol, polyethylene glycol, acrylate polymer, distilled water, fragrance